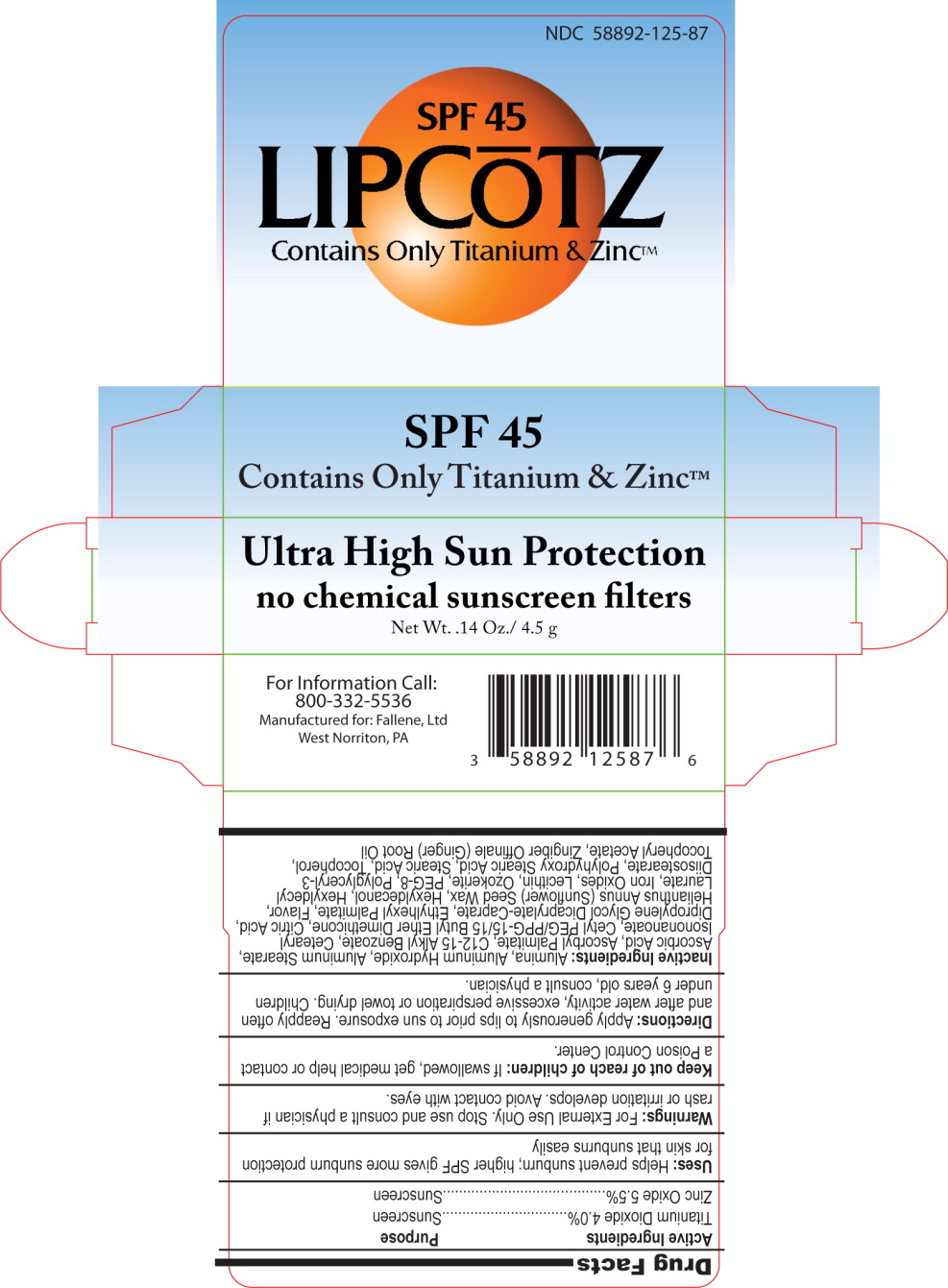 DRUG LABEL: LipCoTZ 
NDC: 58892-125 | Form: LIPSTICK
Manufacturer: Fallien Cosmeceuticals, LTD.
Category: otc | Type: HUMAN OTC DRUG LABEL
Date: 20100909

ACTIVE INGREDIENTS: Titanium Dioxide 40 mg/1 g; Zinc Oxide 55 mg/1 g
INACTIVE INGREDIENTS: Aluminum Oxide; Aluminum Hydroxide; Aluminum Stearate; Ascorbic Acid; Ascorbyl Palmitate; C12-15 Alkyl Benzoate; Ceresin; Cetearyl Isononanoate; Anhydrous Citric Acid; Propylene Glycol Dicaprylate/Dicaprate; Ethylhexyl Palmitate; Kiwi Fruit; Lime (Citrus); Sunflower Oil; Hexyldecanol; Hexyldecyl Laurate; Ferric Oxide Red; Lecithin, Soybean; Polyethylene Glycol 400; Stearic Acid; Alpha-Tocopherol; .ALPHA.-Tocopherol Acetate, D-; Ginger Oil

LIPCŌTZ

Drug Facts

Active Ingredients

Titanium Dioxide 4.0%

Zinc Oxide 5.5%

Purpose

Sunscreen

Sunscreen

Uses:

Helps prevent sunburn; higher SPF gives more sunburn protection for skin that sunburns easily

Warnings:

For External Use Only. Stop use and consult a physician if rash or irritation develops. Avoid contact with eyes.

Keep out of reach of children:

If swallowed, get medical help or contact a Poison Control Center.

Directions:

Apply generously to lips prior to sun exposure. Reapply often and after water activity, excessive perspiration or towel drying. Children under 6 years old, consult a physician.

Inactive Ingredients:

Alumina, Aluminum Hydroxide, Aluminum Stearate, Ascorbic Acid, Ascorbyl Palmitate, C12-15 Alkyl Benzoate, Cetearyl Isononanoate, Cetyl PEG/PPG-15/15 Butyl Ether Dimethicone, Citric Acid, Dipropylene Glycol Dicaprylate-Caprate, Ethylhexyl Palmitate, Flavor, Helianthus Annus (Sunflower) Seed Wax, Hexyldecanol, Hexyldecyl Laurate, Iron Oxides, Lecithin, Ozokerite, PEG-8, Polyglyceryl-3 Diisostearate, Polyhydroxy Stearic Acid, Stearic Acid, Tocopherol, Tocopheryl Acetate, Zingiber Offinale (Ginger) Root Oil

Principal Display Panel – Carton Label

NDC 58892-125-87

SPF 45

LIPCŌTZ

Contains Only Titanium & Zinc™

SPF 45

Contains Only Titanium & Zinc™

Ultra High Sun Protection no chemical sunscreen filters

Net Wt. .14 Oz./ 4.5 g

For Information Call:

800-332-5536

Manufactured for: Fallene, Ltd

West Norriton, PA